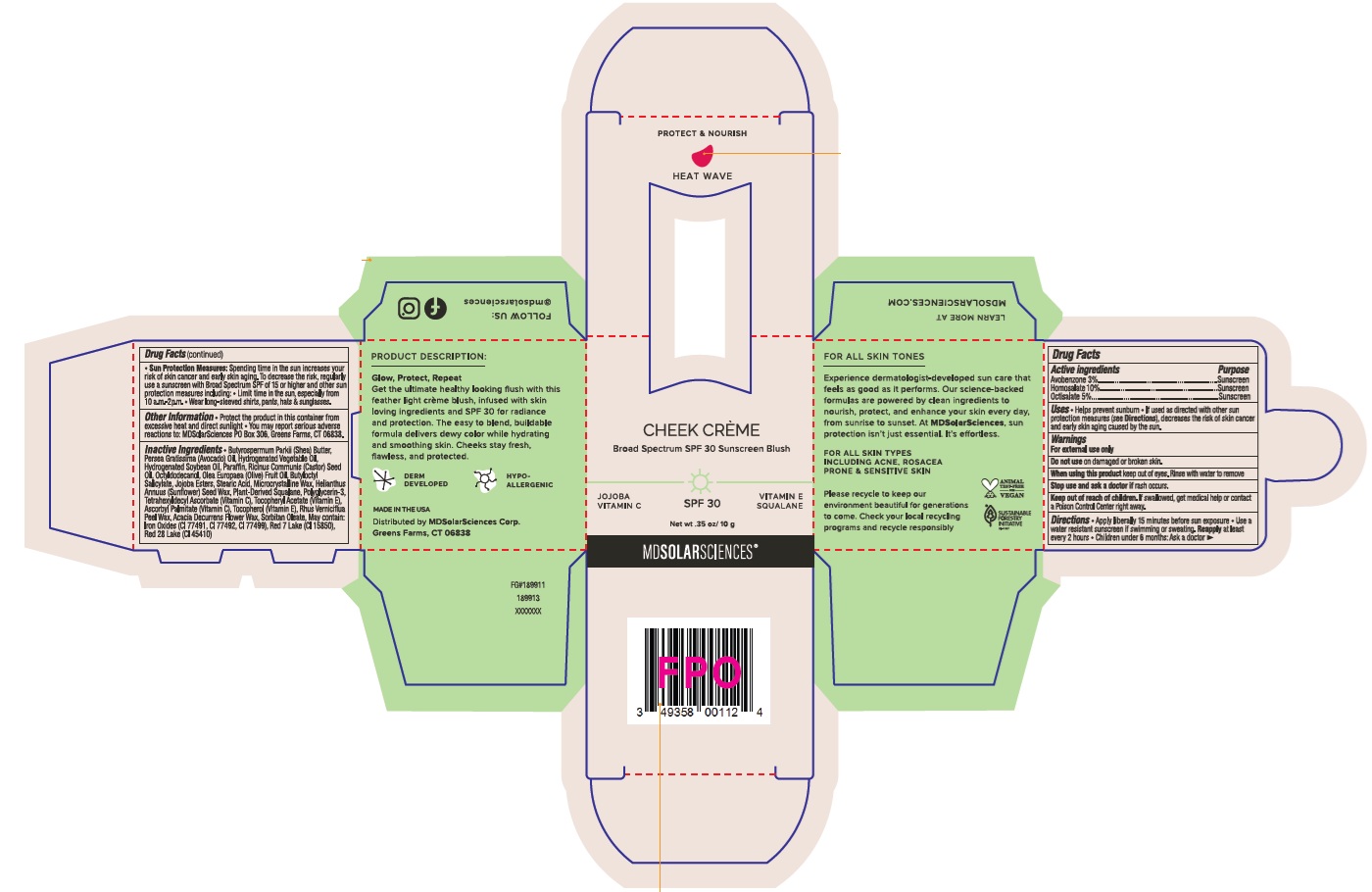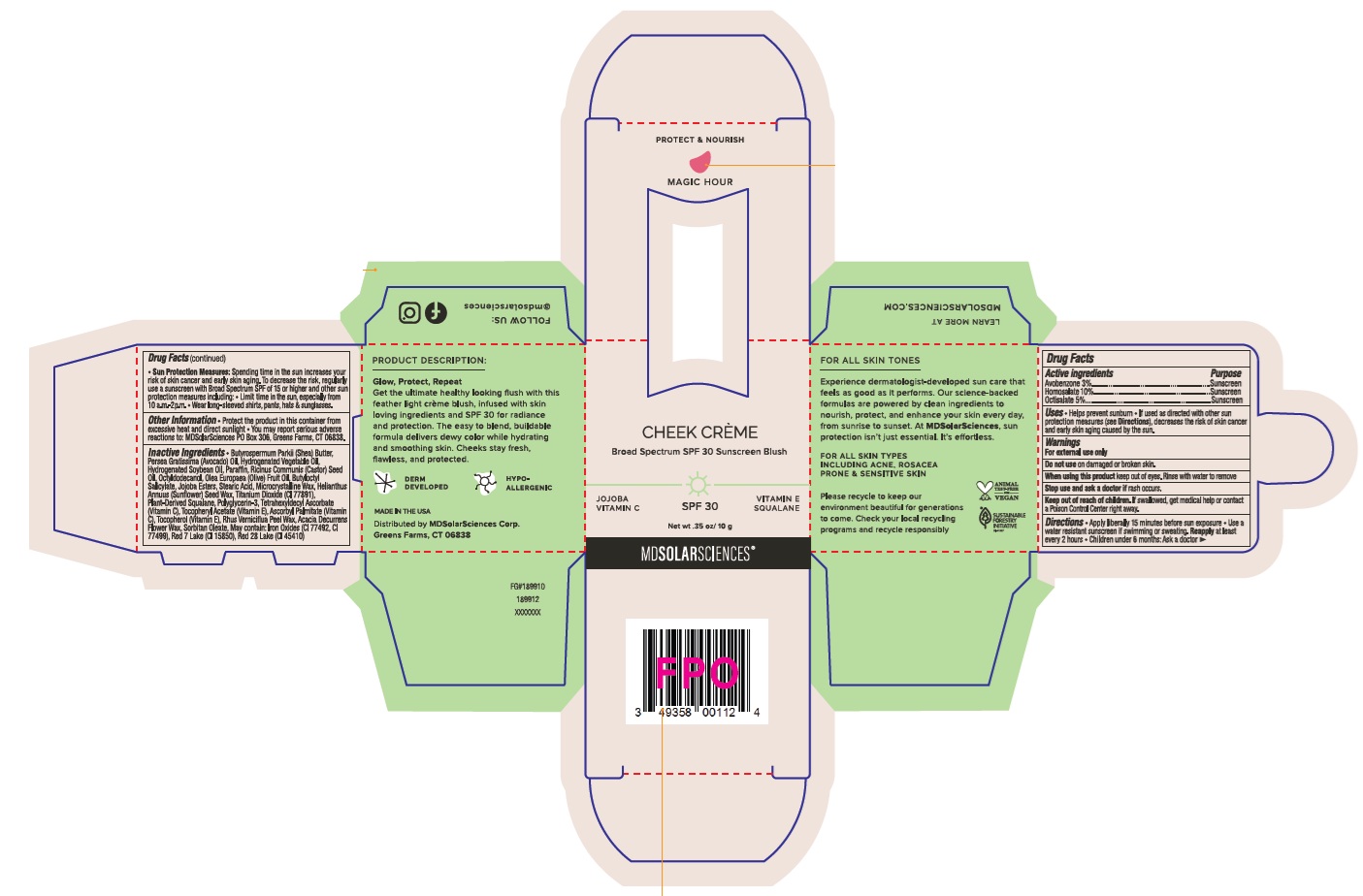 DRUG LABEL: CHEEK CREME BROAD SPECTRUM SPF 30 SUNSCREEN BLUSH HEAT WAVE
NDC: 49358-100 | Form: CREAM
Manufacturer: MDSolarSciences
Category: otc | Type: HUMAN OTC DRUG LABEL
Date: 20250925

ACTIVE INGREDIENTS: AVOBENZONE 30 mg/1 g; HOMOSALATE 100 mg/1 g; OCTISALATE 50 mg/1 g
INACTIVE INGREDIENTS: CI 77499; JOJOBA OIL, RANDOMIZED; TOCOPHEROL; ACACIA DECURRENS FLOWER WAX; SORBITAN OLEATE; TETRAHEXYLDECYL ASCORBATE; ASCORBYL PALMITATE; CI 77492; BUTYLOCTYL SALICYLATE; SHEA BUTTER; AVOCADO OIL; PARAFFIN; HELIANTHUS ANNUUS (SUNFLOWER) SEED WAX; RHUS VERNICIFLUA PEEL WAX; HYDROGENATED SOYBEAN OIL; OCTYLDODECANOL; OLIVE OIL; MICROCRYSTALLINE WAX; SQUALANE; POLYGLYCERIN-3; CI 77491; CI 15850; CI 45410; .ALPHA.-TOCOPHEROL ACETATE; STEARIC ACID; CASTOR OIL

CHEEK CREME BROAD SPECTRUM SPF 30 SUNSCREEN BLUSH

Active ingredients

Avobenzone 3%

Homosalate 10%

Octisalate 5%

Purpose

Sunscreen

Uses

- Helps prevent sunburn
- If used as directed with other sun protection measures (see Directions), decreases the risk of skin cancer and early skin aging caused by the sun.

Warnings

For external use only

Do not use

on damaged or broken skin.

When using this product

keep out of eyes. Rinse with water to remove

Stop use and ask a doctor if

rash occurs.

Keep out of reach of children.

If swallowed, get medical help or contact a Poison Control Center right away.

Directions

- Apply liberally 15 minutes before sun exposure
- Use a water resistant sunscreen if swimming or sweating
- Reapply at least every 2 hours
- Children under 6 months: Ask a doctor
- Sun Protection Measures: Spending time in the sun increases our risk of skin cancer and early skin aging. To decrease the risk, regularly use a sunscreen with Broad Spectrum SPF of 15 or higher and other sun protection measures including:
- Limit time in the sun, especially from 10 a.m. - 2 p.m.
- Wear long-sleeved shirts, pants, hats & sunglasses

Other information

- Protect the product in this container from excessive heat and direct sunlight
- You may report serious adverse reactions to: MDSolarSciences PO Box 306, Greens Farms, CT 06838

Inactive ingredients

Butyrospermum Parkii (Shea) Butter, Persea Gratissima (Avocado) Oil, Hydrogenated Vegetable Oil, Hydrogenated Soybean Oil, Paraffin, Ricinus Communis (Castor) Seed Oil, Octyldodecanol, Olea Europaea (Olive) Fruit Oil, Butyloctyl Salicylate, Jojoba Esters, Stearic Acid, Microcrystalline Wax, Helianthus Annuus (Sunflower) Seed Wax, Plant-Derived Squalane, Polyglycerin-3, Tetrahexyldecyl Ascorbate (Vitamin C), Tocopheryl Acetate (Vitamin E), Ascorbyl Palmitate (Vitamin C), Tocopherol (Vitamin E), Rhus Verniciflua Peel Wax, Acacia Decurrens Flower Wax, Sorbitan Oleate, May contain: Iron Oxides (CI 77491, CI 77492, CI 77499), Red 7 Lake (CI 15850), Red 28 Lake (CI 45410).